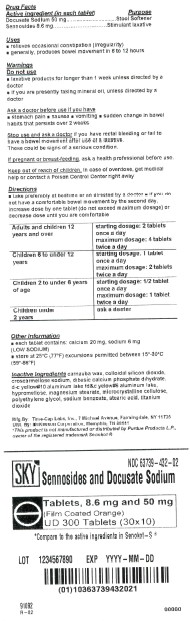 DRUG LABEL: Sennosides and Docusate Sodium
NDC: 63739-432 | Form: TABLET
Manufacturer: McKesson Packaging Services a business unit of McKesson Corporation
Category: otc | Type: HUMAN OTC DRUG LABEL
Date: 20210728

ACTIVE INGREDIENTS: SENNOSIDES A AND B 8.6 mg/1 1; DOCUSATE SODIUM 50 mg/1 1
INACTIVE INGREDIENTS: CARNAUBA WAX; SILICON DIOXIDE; D&C YELLOW NO. 10; FD&C YELLOW NO. 6; HYPROMELLOSES; MAGNESIUM STEARATE; CELLULOSE, MICROCRYSTALLINE; POLYETHYLENE GLYCOL, UNSPECIFIED; SODIUM BENZOATE; STEARIC ACID; TITANIUM DIOXIDE

Drug Facts

Active ingredient

Docusate Sodium 50mg

Sennosides 8.6 mg

Purpose

Docusate Sodium...............Stool Softener

Sennosides.........................Stimulant Laxative

Uses

- relieves occasional constipation (irregularity)
- generally produces bowel movement in 6 to 12 hours

Warnings

Do Not Use

- this product if you are presently taking mineral oil, unless directed by a doctor
- laxative products for longer than 1 week unless directed by a doctor

Ask a doctor before use if you have

- stomach pain
- nausea
- vomiting
- a sudden change in bowel movements that persists over 2 weeks

Stop use and ask a doctor if

- You have rectal bleeding or fail to have a bowel movement after use of a laxative. These could be signs of a serious condition.
- If pregnant or breast -feeding, ask a health professional before use.
- Keep out of reach of children. In case of overdose, get medical help or contact a Poison Control Center right away

Directions

- Take preferably at bedtime or as directed by a doctor
- If you do not have a comfortable bowel movement by the second day, increase dose by one tablet (do not exceed the maximum dosage) or decrease dose until you are comfortable.

Age | Starting Dose | Maximum Dose
Adults and children 12 years of age and over | 2 tablets once a day | 4 tablets twice a day
Children 6 to under 12 years | 1 tablet once a day | 2 tablets twice a day
Children 2 to under 6 years | 1/2 tablet once a day | 1 tablets twice a day
Children under 2 years | ask a doctor | ask a doctor

Other Information

- each tablet contains calcium 20mg, sodium 6mg (LOW SODIUM)
- store at 25°C (77°F) excursions permitted between 15°-30°C (59°-86°F)

Inactive ingredients

carnauba wax, colloidal silicon dioxide, croscarmellose sodium, dibasic calcium phosphate dihydrate, D&C yellow #10 aluminum lake, FD&C yellow #6 aluminum lake, hypromellose, magnesium stearate, microcrystalline cellulose, polyethylene glycol, sodium benzoate, stearic acid, titanium dioxide